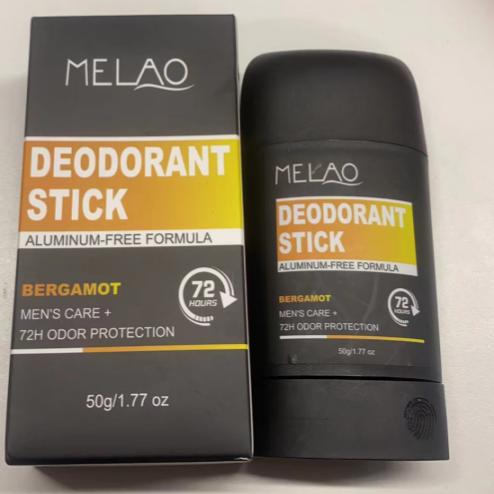 DRUG LABEL: Deodorant Stick
NDC: 83566-566 | Form: STICK
Manufacturer: Guangzhou Yilong Cosmetics Co., Ltd
Category: otc | Type: HUMAN OTC DRUG LABEL
Date: 20240807

ACTIVE INGREDIENTS: PENTAMETHYL CYCLOPENTASILOXANE 56.2 g/100 g; GLYCERYL STEARATE SE 3 g/100 g
INACTIVE INGREDIENTS: .ALPHA.-BISABOLOL, (+)-; TOCOPHEROL; PROPYLPARABEN

Deodorant Stick

Active ingredients

Cyclopentasiloxane 56.20%

Magnesium Hydroxide 12%

Purpose

Deodorization

Uses

STEP1: Clean and thoroughly dry your skin.

STEP2: Twist the bottom of the product.

STEP3: Gently apply to the underarms or other desired areas.

Warnings

For extemnal use only

Stop use and ask a doctor if

rash occurs

Do not use

on damaged or broken skin

When using this product

keep out of eyes. Rinse with water to remove.

Keep out of reach of children.

If swallowed, get medical help or contact a Poison Control Center right away.

INACTIVE INGREDIENT

Beeswax 8%

Ozokerite 5%

Paraffin 3%

Cocos Nucifera(Coconut) Oil 3%

Glyceryl Stearate 3%

Sorbitan Stearate 3%

Aroma 2%

Tocopherol 2%

Propylparaben 0.80%

Bisabolol 1%

BHT 1%

Tocopherol 2%

DOSAGE AND ADMINISTRATION

Twist out an appropriate amount of deodorizing stick and apply it evenly to the skin